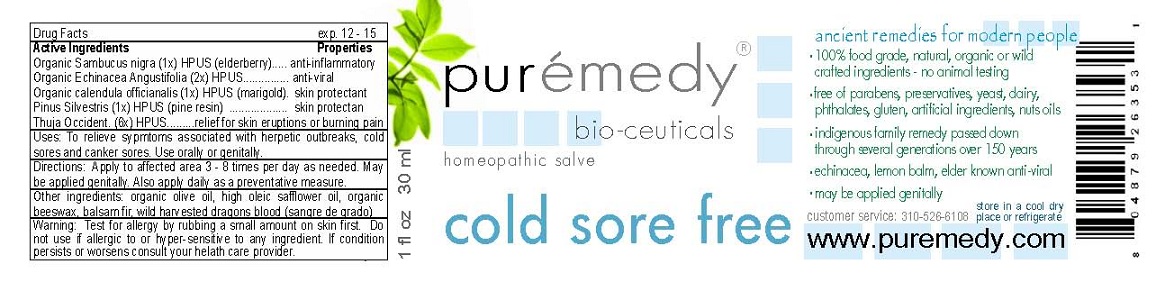 DRUG LABEL: COLD SORE FREE
NDC: 52810-301 | Form: SALVE
Manufacturer: PUREMEDY
Category: homeopathic | Type: HUMAN OTC DRUG LABEL
Date: 20211219

ACTIVE INGREDIENTS: ECHINACEA ANGUSTIFOLIA 2 [hp_X]/100 mL; SAMBUCUS NIGRA FLOWER 1 [hp_X]/100 mL; CALENDULA OFFICINALIS FLOWER 1 [hp_X]/100 mL; PINE NEEDLE OIL (PINUS SYLVESTRIS) 1 [hp_X]/100 mL; THUJA OCCIDENTALIS ROOT 6 [hp_X]/100 mL
INACTIVE INGREDIENTS: OLIVE OIL; SAFFLOWER OIL; YELLOW WAX; ABIES BALSAMEA LEAF OIL; DRAGON'S BLOOD

COLD SORE FREE (52810-301)

ACTIVE INGREDIENTS

ORGANIC SAMBUCUS NIGRA (1X) HPUS (ELDERBERRY)

ORGANIC ECHINACEA ANGUSTIFOLIA (2X) HPUS

ORGANIC CALENDULA OFFICINALIS (1X) HPUS (MARIGOLD)

PINUS SILVESTRIS (1X) HPUS (PINE RESIN)

THUJA OCCIDENT (6X) HPUS

PURPOSE

PROPERTIES

ANTI-INFLAMMATORY

ANTI-VIRAL

SKIN PROTECTANT

SKIN PROTECTANT

RELIEF FOR SKIN ERUPTIONS OR BURNING PAIN

INDICATIONS AND USAGE

USES: TO RELIEVE SYMPTOMS ASSOCIATED WITH HERPETIC OUTBREAKS, COLD SORES AND CANKER SORES. USE ORALLY OR GENITALLY.

DOSAGE AND ADMINISTRATION

DIRECTIONS: APPLY TO AFFECTED AREA 3-8 TIMES PER DAY AS NEEDED. MAY BE APPLIED GENITALLY. ALSO APPLY DAILY AS A PREVENTIVE MEASURE.

INACTIVE INGREDIENT

OTHER INGREDIENTS: ORGANIC OLIVE OIL, HIGH OLEIC SAFFLOWER OIL, ORGANIC BEESWAX, BALSAM FIR, WILD HARVESTED DRAGONS BLOOD (SANGRE DE GRADO).

WARNINGS

WARNING: TEST FOR ALLERGY BY RUBBING A SMALL AMOUNT ON SKIN FIRST. DO NOT USE IF ALLERGIC TO OR HYPER-SENSITIVE TO ANY INGREDIENT IN THIS SALVE. IF CONDITION PERSISTS OR WORSENS CONSULT YOUR HEALTH CARE PROVIDER.

KEEP OUT OF REACH OF CHILDREN.

OTHER SAFETY INFORMATION

STORE IN A COOL DRY PLACE OR REFRIGERATE